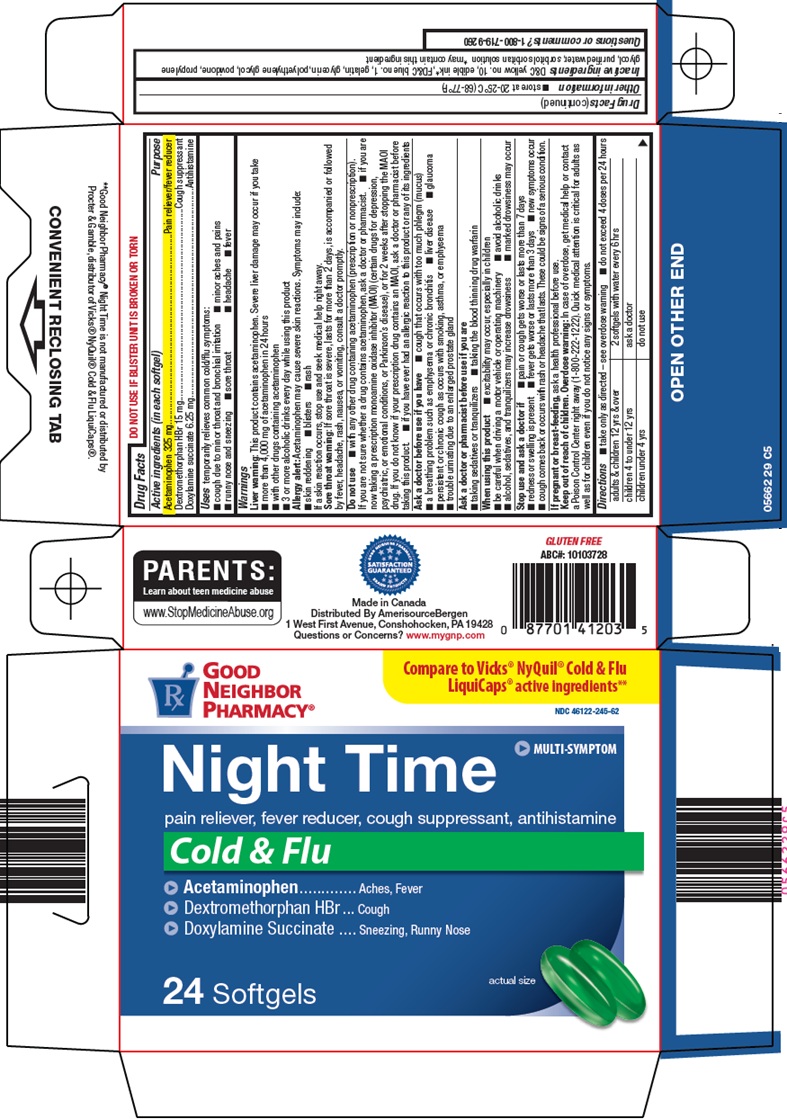 DRUG LABEL: Good Neighbor Pharmacy Night Time
NDC: 46122-245 | Form: CAPSULE, LIQUID FILLED
Manufacturer: Amerisource Bergen
Category: otc | Type: HUMAN OTC DRUG LABEL
Date: 20260119

ACTIVE INGREDIENTS: ACETAMINOPHEN 325 mg/1 1; DEXTROMETHORPHAN HYDROBROMIDE 15 mg/1 1; DOXYLAMINE SUCCINATE 6.25 mg/1 1
INACTIVE INGREDIENTS: D&C YELLOW NO. 10; FD&C BLUE NO. 1; GELATIN, UNSPECIFIED; GLYCERIN; POLYETHYLENE GLYCOL, UNSPECIFIED; POVIDONE, UNSPECIFIED; PROPYLENE GLYCOL; WATER; SORBITOL SOLUTION; SORBITAN

Amerisource Bergen Night Time Drug Facts

Active ingredients (in each softgel)

Acetaminophen 325 mg

Dextromethorphan HBr 15 mg

Doxylamine succinate 6.25 mg

Purpose

Pain reliever/fever reducer

Cough suppressant

Antihistamine

Uses

temporarily relieves common cold/flu symptoms:

- cough due to minor throat and bronchial irritation
- minor aches and pains
- runny nose and sneezing
- sore throat
- headache
- fever

Warnings

Liver warning: This product contains acetaminophen. Severe liver damage may occur if you take

- more than 4,000 mg of acetaminophen in 24 hours
- with other drugs containing acetaminophen
- 3 or more alcoholic drinks every day while using this product

Allergy alert: Acetaminophen may cause severe skin reactions. Symptoms may include:

- skin reddening
- blisters
- rash

If a skin reaction occurs, stop use and seek medical help right away.

Sore throat warning: If sore throat is severe, lasts for more than 2 days, is accompanied or followed by fever, headache, rash, nausea, or vomiting, consult a doctor promptly.

Do not use

- with any other drug containing acetaminophen (prescription or nonprescription). If you are not sure whether a drug contains acetaminophen, ask a doctor or pharmacist.
- if you are now taking a prescription monoamine oxidase inhibitor (MAOI) (certain drugs for depression, psychiatric, or emotional conditions, or Parkinson’s disease), or for 2 weeks after stopping the MAOI drug. If you do not know if your prescription drug contains an MAOI, ask a doctor or pharmacist before taking this product.
- if you have ever had an allergic reaction to this product or any of its ingredients

Ask a doctor before use if you have

- cough that occurs with too much phlegm (mucus)
- a breathing problem such as emphysema or chronic bronchitis
- liver disease
- glaucoma
- persistent or chronic cough as occurs with smoking, asthma, or emphysema
- trouble urinating due to an enlarged prostate gland

Ask a doctor or pharmacist before use if you are

- taking sedatives or tranquilizers
- taking the blood thinning drug warfarin

When using this product

- excitability may occur, especially in children
- be careful when driving a motor vehicle or operating machinery
- avoid alcoholic drinks
- alcohol, sedatives, and tranquilizers may increase drowsiness
- marked drowsiness may occur

Stop use and ask a doctor if

- pain or cough gets worse or lasts more than 7 days
- redness or swelling is present
- fever gets worse or lasts more than 3 days
- new symptoms occur
- cough comes back or occurs with rash or headache that lasts. These could be signs of a serious condition.

If pregnant or breast-feeding,

ask a health professional before use.

Keep out of reach of children.

Overdose warning: In case of overdose, get medical help or contact a Poison Control Center right away (1-800-222-1222). Quick medical attention is critical for adults as well as for children even if you do not notice any signs or symptoms.

Directions

- take only as directed – see overdose warning
- do not exceed 4 doses per 24 hours

adults & children 12 yrs & over | 2 softgels with water every 6 hrs
children 4 to under 12 yrs | ask a doctor
children under 4 yrs | do not use

Other information

- store at 20-25°C (68-77°F)

Inactive ingredients

D&C yellow no. 10, edible ink*, FD&C blue no. 1, gelatin, glycerin, polyethylene glycol, povidone, propylene glycol, purified water, sorbitol sorbitan solution *may contain this ingredient

Questions or comments?

1-800-719-9260

Package/Label Principal Display Panel

GOOD NEIGHBOR PHARMACY®

Compare to Vicks® NyQuil® Cold & Flu LiquiCaps® active ingredients

MULTI-SYMPTOM

Night Time

pain reliever, fever reducer, cough suppressant, antihistamine

Cold & Flu

- Acetaminophen - Aches, Fever

- Dextromethorphan HBr - Cough

- Doxylamine Succinate - Sneezing, Runny Nose

24 Softgels

actual size